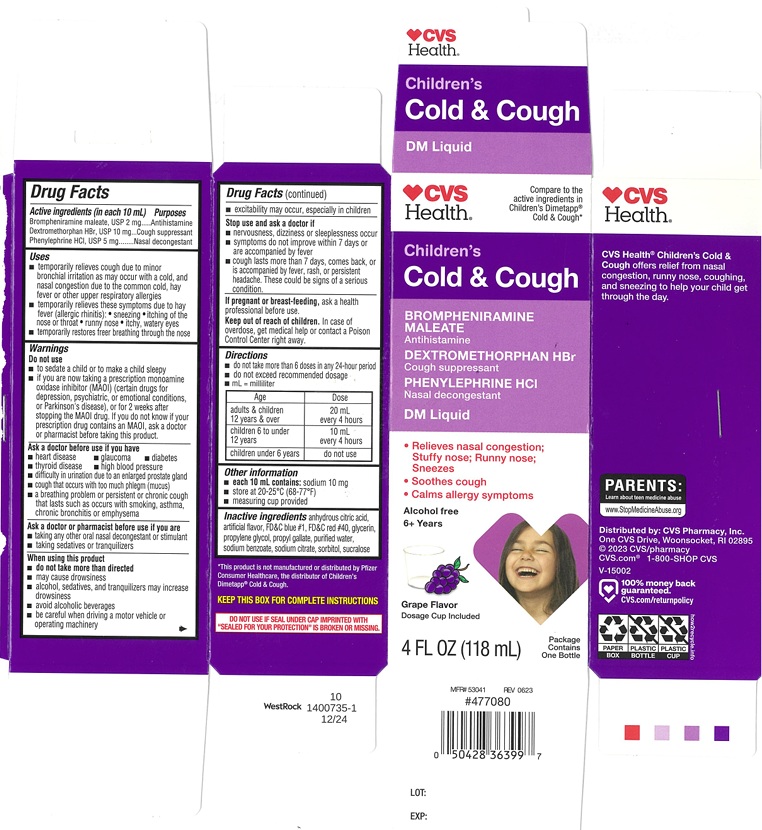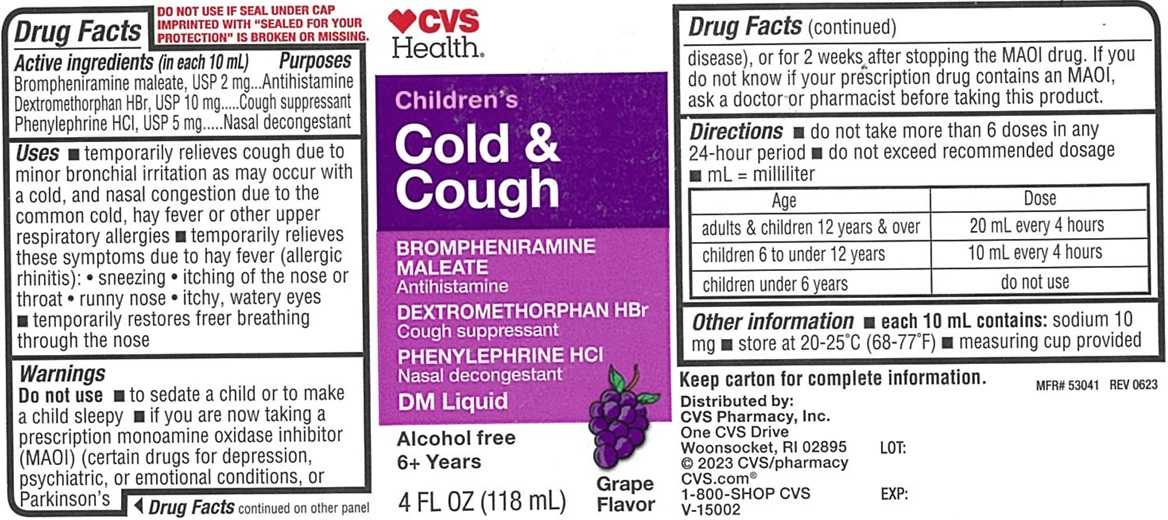 DRUG LABEL: Childrens Cold and Cough
NDC: 51316-578 | Form: LIQUID
Manufacturer: CVS
Category: otc | Type: Human OTC Drug Label
Date: 20250117

ACTIVE INGREDIENTS: BROMPHENIRAMINE MALEATE 2 mg/10 mL; DEXTROMETHORPHAN HYDROBROMIDE 10 mg/10 mL; PHENYLEPHRINE HYDROCHLORIDE 5 mg/10 mL
INACTIVE INGREDIENTS: ANHYDROUS CITRIC ACID; FD&C BLUE NO. 1; FD&C RED NO. 40; GLYCERIN; PROPYLENE GLYCOL; WATER; SODIUM BENZOATE; SORBITOL; SUCRALOSE; PROPYL GALLATE; SODIUM CITRATE

Childrens Cold and Cough 577

ACTIVE INGRADIENTS (in each 10 mL)

Brompheniramine maleate, USP 2 mg

Dextromethorphan HBr, USP 10 mg

Phenylephrine HCl, USP 5 mg

PURPOSES

Antihistamine

Cough Suppressant

Nasal decongestant

USES

- temporarily relieves cough due to minor bronchial irritation as may occur with a cold, and nasal congestion due to the common cold, hay fever or other upper respiratory allergies

- temporarily relieves these symptoms due to hay fever (allergic rhinitis):

- sneezing
- Itching of the nose or throat
- runny nose
- itchy, watery eyes

- temporarily restores freer breathing through the nose

WARNINGS

.

DO NOT USE

- to sedate a child or to make a child sleepy

- if you are now taking a prescription monoamine oxidase inhibitor (MAOI) (certain drugs for depression, or psychiatric, for 2 weeks after stopping the MAOI drug. If you do not know if your prescription drug contains an MAOI, ask a doctor or pharmacist before taking this product.

ASK A DOCTOR BEFORE USE IF YOU HAVE

- heart disease
- glaucoma
- diabetes
- thyroid disease
- high blood pressure
- difficulty in urination due to an enlarged prostate gland
- cough that occurs with too much phlegm (mucus)
- a breathing problem or persistent or chronic cough that lasts such as occurs with smoking, asthma, chronic bronchitis or emphysema

ASK A DOCTOR OR PHARMACIST BEFORE USE IF YOU ARE

- taking any other oral nasal decongestant or stimulant
- taking sedative or tranquilizers

WHEN USING THIS PRODUCT

- do not take more than directed
- may cause drowsiness
- alcohol, sedatives, and tranquillizers may increase drowsiness
- avoid alcoholic beverages
- be careful when driving a motor vehicle or operating machinery
- excitability may occur, especially in children

STOP USE AND ASK A DOCTOR IF

- nervousness, dizziness or sleeplessness occur
- symptoms do not improve within 7 days or are accompanied by fever
- cough lasts more than 7 days, comes back, or is accompanied by fever, rash, or persistent headache. These could be signs of a serious condition.

IF PREGNANT OR BREAST-FEEDING,

ask a health professional before use.

KEEP OUT OF REACH OF CHILDREN.

In case of overdose, get medical help or contact a Poison Control Center right away.

DIRECTIONS

- do not take more than 6 doses in any 24-hour period
- measure only with dosing cup provided
- do not exceed recommended dosage
- mL = milliliter

Age | Dose
adults & children 12 years & over | 20 mL every 4 hours
children 6 to under 12 years | 10 mL every 4 hours
children under 6 years | do not use

OTHER INFORMATION

- each 10 mL contains: sodium 10 mg
- store at 20-25ºC (68-77ºF)
- measuring cup provided

INACTIVE INGREDIENTS

anhydrous citric acid, artificial flavor, FD&C blue #1, FD&C Red #40, glycerin, propylene glycol, propyl gallate, purified water, sodium benzoate, sodium citrate, sorbitol, sucralose

PRINCIPAL DISPLAY PANEL

CVS

Health ®

Compare to the active ingredients in Children's Dimetapp® Cold & Cough*

NDC 51316-578-03

Children's

Cold & Cough

BROMPHENIRAMIINE MALEATE

Antihistamine

DEXTROMETHORPHAN HYDROBROMIDE

Cough Suppressant

PHENYLEPHRINE HYDROCHLORIDE

Nasal Decongestant

DM Liquid

- Relieves nasal congestion;
  Stuffy nose; Runny nose;
  Sneezes
- Soothes Cough
- Calm allergy symptoms

Alcohol free

6+ Years

Grape Flavor

Dosage Cup Included

4 FL OZ (118 mL)